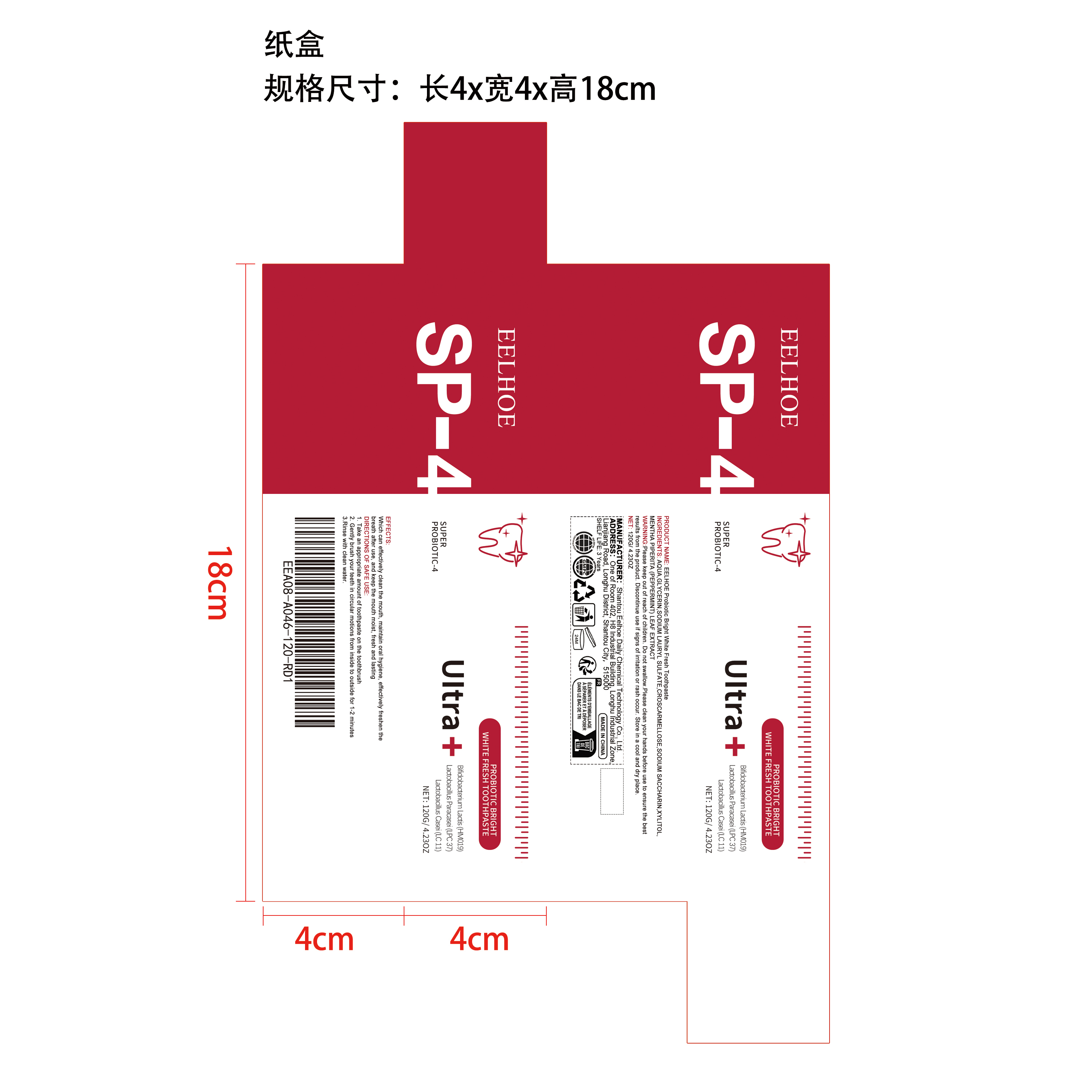 DRUG LABEL: EELHOE Probiotic Bright White Fresh
NDC: 85064-016 | Form: CREAM
Manufacturer: Shantou Eelhoe Daily Chemical Technology Co., Ltd.
Category: otc | Type: HUMAN OTC DRUG LABEL
Date: 20251127

ACTIVE INGREDIENTS: MENTHA PIPERITA (PEPPERMINT) LEAF 0.024 mg/120 mg
INACTIVE INGREDIENTS: XYLITOL 0.6 mg/120 mg; SODIUM SACCHARIN 0.6 mg/120 mg; SODIUM LAURYL SULFATE 4.8 mg/120 mg; AQUA 98.376 mg/120 mg; GLYCERIN 12 mg/120 mg; CROSCARMELLOSE 3.6 mg/120 mg

Active Ingredient(s)

MENTHA PIPERITA (PEPPERMINT) LEAF EXTRACT

Purpose

Which can effectively clean the mouth, maintain oral hygiene, effectively freshen the breath after use, and keep the mouth moist, fresh and lasting

Use

1.Take an appropriate amount of toothpaste on the toothbrush

2.Gently brush your teeth in circular motions from inside to outside for 1-2 minutes

3.Rinse with clean water.

Warnings

Please keep out of reach of children. Do not swallow.Please clean your hands before use to ensure the best results from the product. Discontinue use if signs of irritation or rash occur. Store in a cool and dry place.

Do not use

Discontinue use if signs of irritation or rash occur.

STOP USE

Discontinue use if signs of irritation or rash occur.

KEEP OUT OF REACH OF CHILDREN

Please keep out of reach of children. Do not swallow.

STORAGE AND HANDLING

Store in a cool and dry place.

INACTIVE INGREDIENT

AQUA、GLYCERIN、SODIUM LAURYL SULFATE、CROSCARMELLOSE、SODIUM SACCHARIN、XYLITOL

INDICATIONS AND USAGE

1. Take an appropriate amount of toothpaste on the toothbrush

2. Gently brush your teeth in circular motions from inside to outside for 1-2 minutes

3.Rinse with clean water.

DOSAGE AND ADMINISTRATION

1. Take an appropriate amount of toothpaste on the toothbrush

2. Gently brush your teeth in circular motions from inside to outside for 1-2 minutes

3.Rinse with clean water.